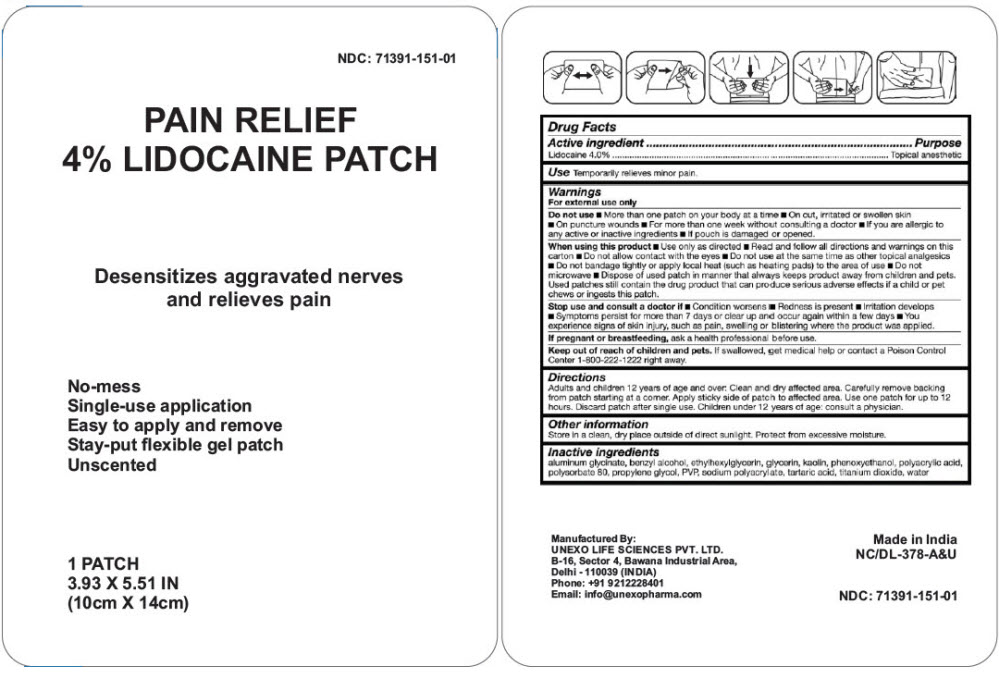 DRUG LABEL: Pain Relief 4% Lidocaine
NDC: 71391-151 | Form: PATCH
Manufacturer: Unexo Life Sciences Private Limited
Category: otc | Type: HUMAN OTC DRUG LABEL
Date: 20250113

ACTIVE INGREDIENTS: Lidocaine 344 mg/1 1
INACTIVE INGREDIENTS: DIHYDROXYALUMINUM AMINOACETATE ANHYDROUS; Benzyl Alcohol; Ethylhexylglycerin; Glycerin; Kaolin; Phenoxyethanol; POLYACRYLIC ACID (250000 MW); Polysorbate 80; Propylene Glycol; POVIDONE, UNSPECIFIED; SODIUM POLYACRYLATE (8000 MW); Tartaric Acid; Titanium Dioxide; Water

Pain Relief 4% Lidocaine Patch

Drug Facts

Active Ingredient

Lidocaine 4.0%

Purpose

Topical anesthetic

Uses

Temporarily relieves minor pain.

Warnings

For external use only

Do not use

- More than one patch on your body at a time
- On cut, irritated or swollen skin
- On puncture wounds
- For more than one week without consulting a doctor
- If you are allergic to any active or inactive ingredients
- If pouch is damaged or opened.

When using this product

- Use only as directed
- Read and follow all directions and warnings on this pack
- Do not allow contact with the eyes
- Do not use at the same time as other topical analgesics
- Do not bandage tightly or apply local heat (such as heating pads) to the area of use
- Do not microwave
- Dispose of used patch in manner that always keeps product away from children and pets
- Used patches still contain the drug product that can produce serious adverse effects if a child or pet chews or ingests this patch

Stop use and ask a doctor if

- Condition worsens
- Redness is present
- Irritation develops
- Symptoms persist for more than 7 days or clear up and occur again within a few days
- You experience signs of skin injury, such as pain, swelling or blistering where the product was applied

PREGNANCY OR BREAST FEEDING

If pregnant or breast-feeding, ask a health professional before use.

Keep out of reach of children. If swallowed, get medical help or contact a Poison Control Center (1-800-222-1222) right away.

Directions

Adults and children over 12 years: Clean and dry affected area. Remove film from patch (see illustration). Apply sticky side of patch to affected area. Use one patch for up to 12 hours. Discard patch after single use

- Children 12 years of age or younger: Consult a physician.

Other Information

Store in a clean, dry place outside of direct sunlight. Protect from excessive moisture.

Inactive Ingredients

aluminum glycinate, benzyl alcohol, ethylhexylglycerin, glycerin, kaolin, methylparaben, phenoxyethanol, polyacrylic acid, polysorbate 80, propylene glycol, propylparaben, PVP, sodium polyacrylate, tartaric acid, titanium dioxide, water

Questions or Comments

Call +91 9212228401

Manufactured By:

UNEXO LIFE SCIENCES PVT. LTD.
B-16. Sector 4, Bawana Industrial Area,
Delhi – 110039 (INDIA)

PRINCIPAL DISPLAY PANEL - One Patch Pouch

NDC: 71391-151-01

PAIN RELIEF
4% LIDOCAINE PATCH

Desensitizes aggravated nerves
and relieves pain

No-mess
Single-use application
Easy to apply and remove
Stay-put flexible gel patch
Unscented

1 PATCH
3.93 X 5.51 IN
(10cm X 14cm)